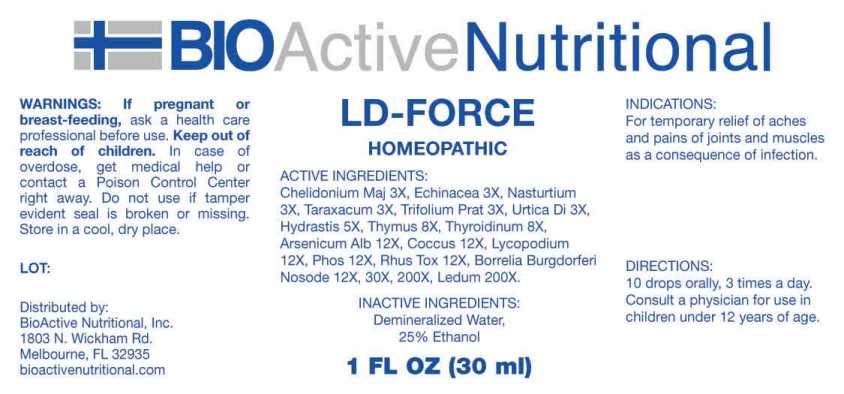 DRUG LABEL: LD Force
NDC: 43857-0653 | Form: LIQUID
Manufacturer: BioActive Nutritional, Inc.
Category: homeopathic | Type: HUMAN OTC DRUG LABEL
Date: 20250107

ACTIVE INGREDIENTS: CHELIDONIUM MAJUS WHOLE 3 [hp_X]/1 mL; ECHINACEA ANGUSTIFOLIA WHOLE 3 [hp_X]/1 mL; WATERCRESS 3 [hp_X]/1 mL; TARAXACUM OFFICINALE 3 [hp_X]/1 mL; TRIFOLIUM PRATENSE FLOWER 3 [hp_X]/1 mL; URTICA DIOICA WHOLE 3 [hp_X]/1 mL; GOLDENSEAL 5 [hp_X]/1 mL; SUS SCROFA THYMUS 8 [hp_X]/1 mL; THYROID 8 [hp_X]/1 mL; ARSENIC TRIOXIDE 12 [hp_X]/1 mL; PROTORTONIA CACTI 12 [hp_X]/1 mL; LYCOPODIUM CLAVATUM SPORE 12 [hp_X]/1 mL; PHOSPHORUS 12 [hp_X]/1 mL; TOXICODENDRON PUBESCENS LEAF 12 [hp_X]/1 mL; BORRELIA BURGDORFERI 12 [hp_X]/1 mL; RHODODENDRON TOMENTOSUM LEAFY TWIG 200 [hp_X]/1 mL
INACTIVE INGREDIENTS: WATER; ALCOHOL

DRUG FACTS:

ACTIVE INGREDIENTS:

Chelidonium Majus 3X, Echinacea 3X, Nasturtium Aquaticum 3X, Taraxacum Officinale 3X, Trifolium Pratense 3X, Urtica Dioica 3X, Hydrastis Canadensis 5X, Thymus 8X, Thyroidinum 8X, Arsenicum Album 12X, Coccus Cacti 12X, Lycopodium Clavatum 12X, Phosphorus 12X, Rhus Tox 12X, Borrelia Burgdorferi Nosode 12X, 30X, 200X, Ledum Palustre 200X.

PURPOSE:

For temporary relief of aches and pains of joints and muscles as a consequence of infection.

WARNINGS:

If pregnant or breast-feeding, ask a health care professional before use.

Keep out of reach of children. In case of overdose, get medical help or contact a Poison Control Center right away.

Do not use if tamper evident seal is broken or missing.

Store in a cool, dry place.

KEEP OUT OF REACH OF CHILDREN:

In case of overdose, get medical help or contact a Poison Control Center right away.

DIRECTIONS:

10 drops orally, 3 times a day. Consult a physician for use in children under 12 years of age.

INDICATIONS:

For temporary relief of aches and pains of joints and muscles as a consequence of infection.

INACTIVE INGREDIENTS:

Demineralized Water, 25% Ethanol

QUESTIONS:

Distributed by:

BioActive Nutritional, Inc.

1803 N. Wickham Rd.

Melbourne, FL 32935

bioactivenutritional.com

PACKAGE LABEL DISPLAY:

BioActiveNutritional

LD-FORCE

HOMEOPATHIC

1 FL OZ (30 ml)